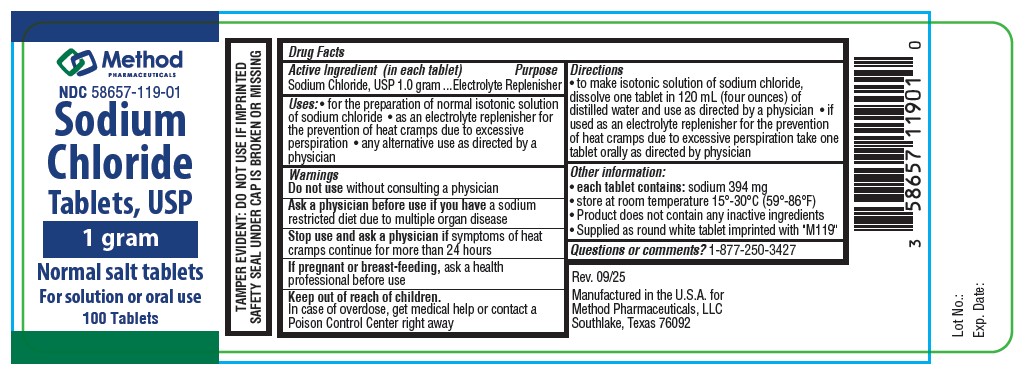 DRUG LABEL: Sodium Chloride
NDC: 58657-119 | Form: TABLET
Manufacturer: Method Pharmaceuticals, LLC
Category: otc | Type: HUMAN OTC DRUG LABEL
Date: 20260217

ACTIVE INGREDIENTS: SODIUM CHLORIDE 1000 mg/1 1

SODIUM CHLORIDE TABLETS, USP 1 Gram

Drug Facts

Active Ingredient (in each tablet)
Sodium Chloride, USP 1 Gram

Inactive Ingredients

NONE

Purpose

Electrolyte Replenisher

Uses

- for the preparation of normal isotonic solution of sodium chloride
- as an electrolyte replenisher for the prevention of heat cramps due to excessive perspiration
- any alternative use as directed by a physician

Warnings

Do not use without consulting a physician

ASK DOCTOR

Ask a physician before use if you have a sodium restricted diet due to multiple organ diseases

Stop use and ask a physician if symptoms of heat cramps continue for more than 24 hours

PREGNANCY OR BREAST FEEDING

If pregnant or breast-feeding, ask a health professional before use

OVERDOSAGE

In case of overdose, get medical help or contact a Poison Control Center right away.

Directions

- to make isotonic solution of sodium chloride, dissolve one tablet in 120 mL (four ounces) of distilled water and use as directed by a physician
- if used as an electrolyte replenisher for the prevention of heat cramps due to excessive perspiration take one tablet orally as directed by your physician.

Other information:

- each tablet contains: sodium 394 mg
- store at room temperature 15ºC to 30ºC (59ºF to 86ºF)
- Product does not contain any inactive ingredients
- Supplied as round white tablet imprinted with "M119"

Questions or comments?1-877-250-3427

Rev. 09/25

Manufactured in the U.S.A. for

Method Pharmaceuticals, LLC

Southlake, Texas 76092

Package Label

NDC-58657-119-01

Sodium Chloride Tablets, USP

1 gram

Normal salt tablets

For solutins or oral use

100 tablets